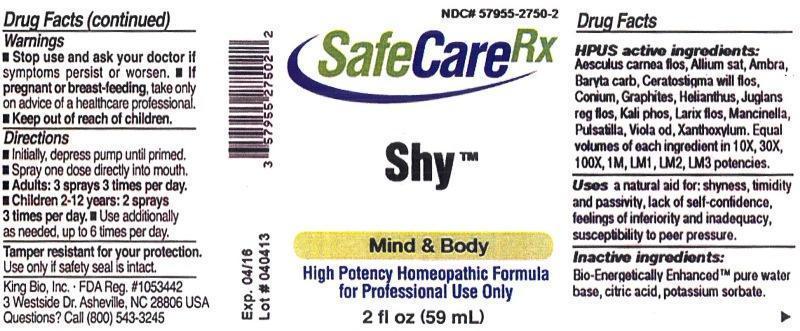 DRUG LABEL: Shy
NDC: 57955-2750 | Form: LIQUID
Manufacturer: King Bio Inc.
Category: homeopathic | Type: HUMAN PRESCRIPTION DRUG LABEL
Date: 20130528

ACTIVE INGREDIENTS: AESCULUS CARNEA FLOWER 10 [hp_X]/59 mL; GARLIC 10 [hp_X]/59 mL; AMBERGRIS 10 [hp_X]/59 mL; BARIUM CARBONATE 10 [hp_X]/59 mL; CERATOSTIGMA WILLMOTTIANUM FLOWER 10 [hp_X]/59 mL; CONIUM MACULATUM FLOWERING TOP 10 [hp_X]/59 mL; GRAPHITE 10 [hp_X]/59 mL; HELIANTHUS ANNUUS FLOWERING TOP 10 [hp_X]/59 mL; JUGLANS REGIA FLOWERING TOP 10 [hp_X]/59 mL; POTASSIUM PHOSPHATE, DIBASIC 10 [hp_X]/59 mL; LARIX DECIDUA FLOWERING TOP 10 [hp_X]/59 mL; HIPPOMANE MANCINELLA FRUITING LEAFY TWIG 10 [hp_X]/59 mL; PULSATILLA VULGARIS 10 [hp_X]/59 mL; VIOLA ODORATA 10 [hp_X]/59 mL; ZANTHOXYLUM AMERICANUM BARK 10 [hp_X]/59 mL
INACTIVE INGREDIENTS: WATER; CITRIC ACID MONOHYDRATE; POTASSIUM SORBATE

Shy
SafeCareRx

Drug Facts

___________________________________________________________________________________________________________________

HPUS active ingredients: Aesculus carnea, flos, allium sativum, Ambra grisea, Baryta carbonica, Ceratostigma willmottianum, flos, Conium maculatum, Graphites, Helianthus annuus, Juglans regia, flos, Kali phosphoricum, Larix decidua, flos, Mancinella, Pulsatilla, Viola odorata, Xanthoxylum fraxineum.

Equal volumes of each ingredient in 10X, 30X, 100X, 1M, LM1, LM2, LM3 potencies.

INDICATIONS AND USAGE

Uses a natural aid for: shyness, timidity and passivity, lack of self-confidence, feeling of inferiority and inadequacy, susceptibility to peer pressure.

Inactive ingredients:

Bio-Energetically Enhanced™ pure water base, citric acid, potassium sorbate.

Warnings

- Stop use and ask your doctor if symptoms persist or worsen.
- If pregnant or breast-feeding, take only on advice of a healthcare professional.

- Keep out of reach of children.

Directions

- Initially, depress pump until primed.
- Spray one dose directly into mouth.
- Adults: 3 sprays 3 times per day.
- Children 2-12 years: 2 sprays 3 times per day.
- Ues additionally as needed, up to 6 times per day

OTHER SAFETY INFORMATION

Tamper resistant for your protection. Use only if safety seal is intact.